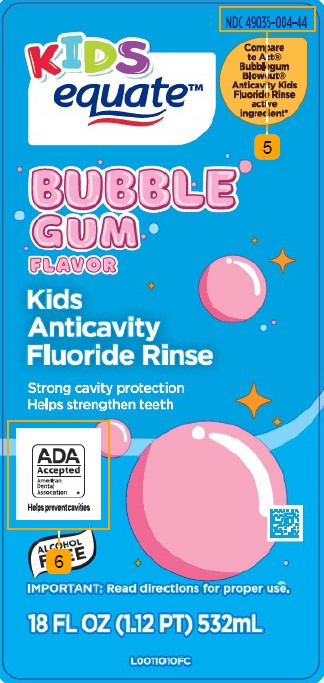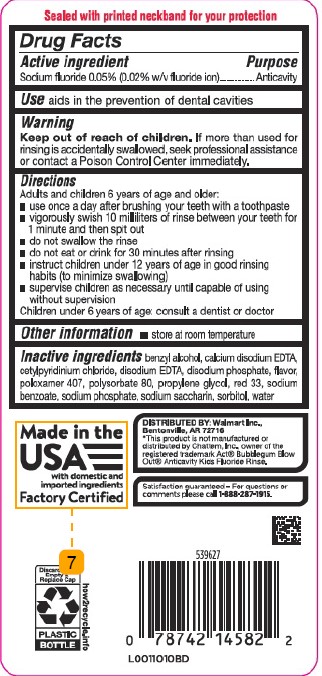 DRUG LABEL: Anticavity Rinse
NDC: 49035-004 | Form: MOUTHWASH
Manufacturer: Walmart Inc.
Category: otc | Type: HUMAN OTC DRUG LABEL
Date: 20260227

ACTIVE INGREDIENTS: SODIUM FLUORIDE 0.2 mg/1 mL
INACTIVE INGREDIENTS: BENZYL ALCOHOL; EDETATE CALCIUM DISODIUM ANHYDROUS; CETYLPYRIDINIUM CHLORIDE; EDETATE DISODIUM; SODIUM PHOSPHATE, DIBASIC, ANHYDROUS; POLOXAMER 407; POLYSORBATE 80; PROPYLENE GLYCOL; D&C RED NO. 33; SODIUM BENZOATE; SODIUM PHOSPHATE; SACCHARIN SODIUM; SORBITOL; WATER

Equate 004.002/004AE
Anticavity Fluoride Rinse, Bubble Gum

Tamper Evident Statement

Sealed with printed neckband for your protection

Active ingredient

Sodium Fluoride 0.05% (0.2% w/v fluoride ion)

Purpose

Anticavity

Use

aids in the prevention of dental cavities

Warnings

for this product

Keep out of reach of children.

If more than used for rinsing is accidentally swallowed, seek professional assistance or contact a Poison Control Center immediately.

Directions

Adults and children 6 year of age and older:

- use once a day after brushing your teeth with a toothpaste
- vigorously swish 10 milliliters of rinse between your teeth for 1 minute and then spit out
- do not swallow the rinse
- do not eat or drink for 30 minutes after rinsing
- instruct children under 12 years of age in good rinsing habits (to minimize swallowing)
- supervise children as necessary until capable of using without supervision

Children under 6 year of age: consult a dentist or doctor

Other information

- store at room temperature

Inactive ingredients

benzyl alcohol, calcium disodium EDTA, cetylpyridinium chloride, disodium EDTA, disodium phosphate, flavor, poloxomer 407, polysorbate 80, propylene glycol, red 33, sodium benzoate, sodium phosphate, sodium saccharin, sorbitol, water

Adverse reaction

Distributed by: Walmart Inc.,

Bentonville, AR 72716

Satisfaction guaranteed - for questions or comments please call 1-888-287-1915

Disclaimer

Made in the USA

with domestic and imported ingredients

Factory Certified

*This product is not manufactured or distributed by Chattem, Inc., owner of the registered trademarks ACT® {and} Bubblegum Blow Out® Anticavity Kids Fluoride Rinse.

Discard Empty & Replace Cap

PLASTIC BOTTLE

how2recycle.info

principal display panel

NDC: 49035-004-44

KIDS

equate™

Compare to ACT® Bubblegum Blowout® Anticavity Kids Fluoride Rinse active ingredient*

BUBBLE GUM FLAVOR

Kids Anticavity Fluoride Rinse

Strong cavity protection

Helps strengthen teeth

ADA Accepted

American Dental Assoication

- Helps prevent cavities

ALCOHOL FREE

IMPORTANT: Read directions for proper use.

18 FL OZ (1.12 PT) 532 mL